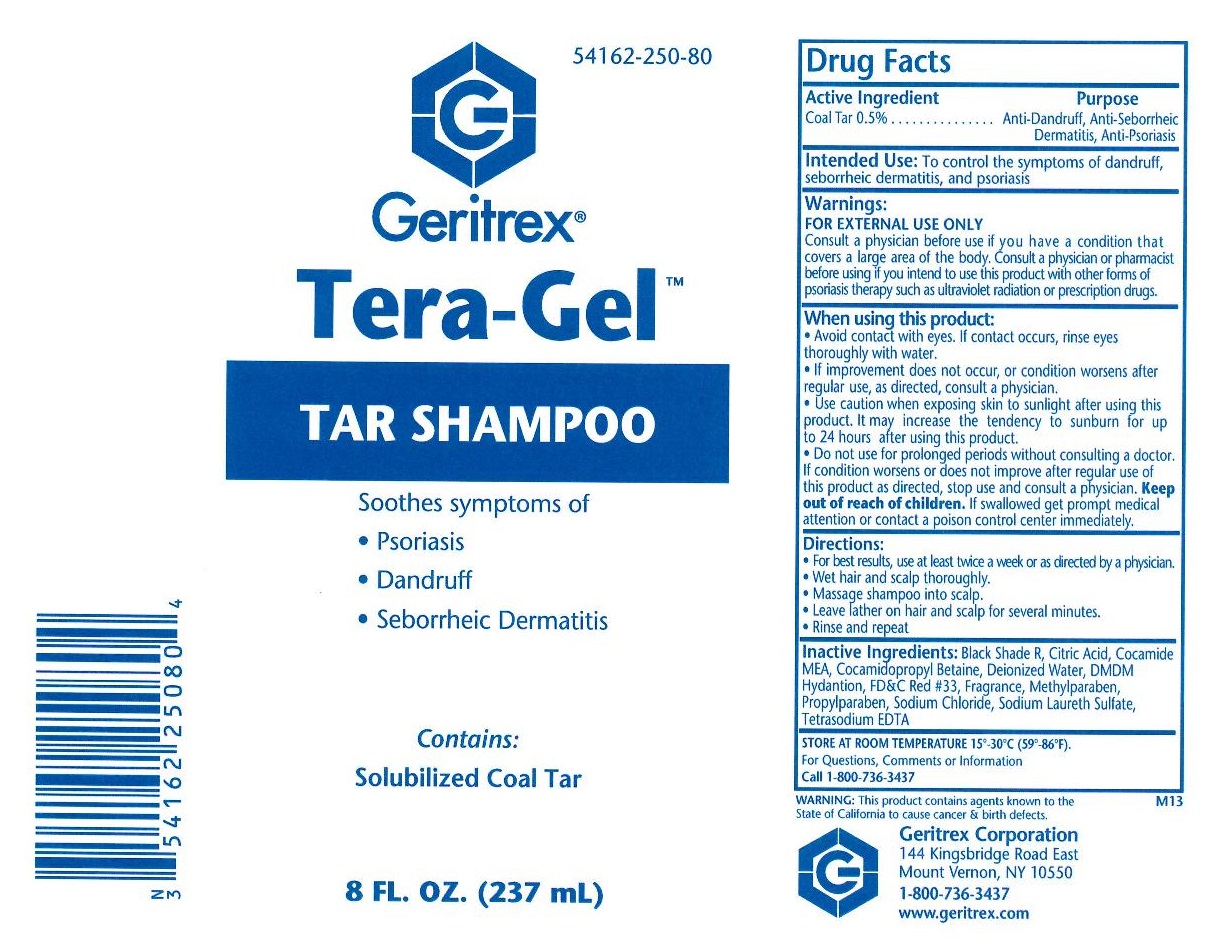 DRUG LABEL: Tera-Gel
NDC: 54162-250 | Form: SHAMPOO
Manufacturer: Geritrex LLC
Category: otc | Type: HUMAN OTC DRUG LABEL
Date: 20160119

ACTIVE INGREDIENTS: COAL TAR 1.365 g/237 mL
INACTIVE INGREDIENTS: WATER; COCO DIETHANOLAMIDE; POLYSORBATE 20; POLYSORBATE 80; CITRIC ACID MONOHYDRATE; COCAMIDOPROPYL BETAINE; DMDM HYDANTOIN; METHYLPARABEN; PROPYLPARABEN; SODIUM CHLORIDE; SODIUM LAURETH SULFATE; EDETATE SODIUM

Tera-Gel Shampoo

Active Ingredient

Active Ingredient Purpose
0.5% Coal Tar . . . . . . . . . . . . . . . Anti-Dandruff, Anti-Seborrheic
Dermatitis, Anti-Psoriasis

Uses

To control the symptoms of dandruff,
seborrheic dermatitis, and psoriasis

Directions

For best results, use at least twice a week or as directed by a physician.
• Wet hair and scalp thoroughly.
• Massage shampoo into scalp.
• Leave lather on hair and scalp for several minutes.
• Rinse and repeat

DOSAGE AND ADMINISTRATION

For best results, use at least twice a week or as directed by a physician.

Warnings

FOR EXTERNAL USE ONLY
Consult a physician before use if you have a condition that
covers a large area of the body. Consult a physician or pharmacist
before using if you intend to use this product with other forms of
psoriasis therapy such as ultraviolet radiation or prescription drugs.
When using this product:
• Avoid contact with eyes. If contact occurs, rinse eyes
thoroughly with water.
• If improvement does not occur, or condition worsens after
regular use, as directed, consult a physician.
• Use caution when exposing skin to sunlight after using this
product. It may increase the tendency to sunburn for up
to 24 hours after using this product.
• Do not use for prolonged periods without consulting a doctor.
If condition worsens or does not improve after regular use of
this product as directed, stop use and consult a physician.

STORAGE AND HANDLING

15°-30°C (59°-86°F).

Keep out of reach of children. If swallowed get prompt medical
attention or contact a poison control center immediately.

Inactive Ingredients:

Black Shade R, Citric Acid, Cocamide MEA, Cocamidopropyl Betaine, Deionized Water, DMDM Hydantoin, FD&C Red #33, Fragrance, Methylparaben, Propylparaben, Sodium Chloride, Sodium Laureth Sulfate, Tetrasodium EDTA.